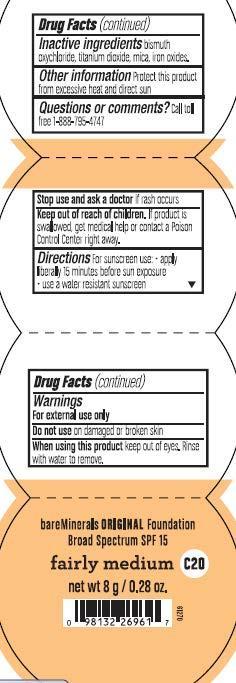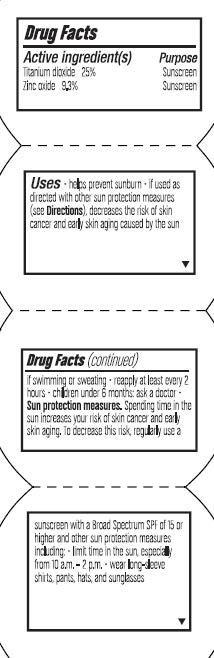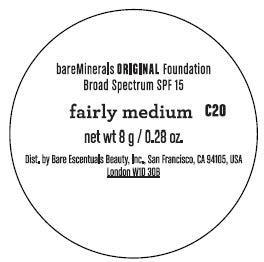 DRUG LABEL: Fairly Medium Foundation SPF 15
NDC: 98132-924 | Form: POWDER
Manufacturer: Bare Escentuals Beauty Inc.
Category: otc | Type: HUMAN OTC DRUG LABEL
Date: 20130204

ACTIVE INGREDIENTS: Zinc Oxide 9.3 g/100 g; Titanium Dioxide 25 g/100 g
INACTIVE INGREDIENTS: MICA; BISMUTH OXYCHLORIDE; BROWN IRON OXIDE; FERRIC OXIDE YELLOW

BareMineral Original SPF 15 Foundation Fairly Medium

Drug Facts

Active Ingredients

Zinc Oxide 9.3%
Titanium Dioxide 25%

Purpose

Sunscreen
Sunscreen

Uses

- Helps prevent sunburn
- If used as directed with other sun protection measures (see Directions), decreases the risk of skin cancer and early skin aging caused by the sun

Warnings

For External use only

- Do not use on damage or broken skin
- When using this product keep out of eyes. Rinse with water to remove
- Stop use and ask doctor if rash occurs
- Keep out of reach of children
- If product is swallowed get medical help or contact a poison control center right away

Directions

- Apply liberally 15 minutes before sun exposure
- Use a water-resistant sunscreen if swimming or sweating
- reapply at least every 2 hours
- children under 6 months: ask a doctor
- Sun protection measures. Spending time in the sun increases your risk of skin cancer or early skin aging. To decrease this risk, regularly use a a sunscreen with a broad spectrum SPF of 15 or higher and other sun protection measures including:
- Limit time in the sun, especially from 10 a.m. - 2 p.m.
- Wear long sleeve shirts, pants, hats, and sunglasses

Inactive Ingredients

Bismuth Oxychloride, Iron Oxides, Mica, Titanium Dioxide

Questions or Comments?

Call toll free 1-888-795-4747